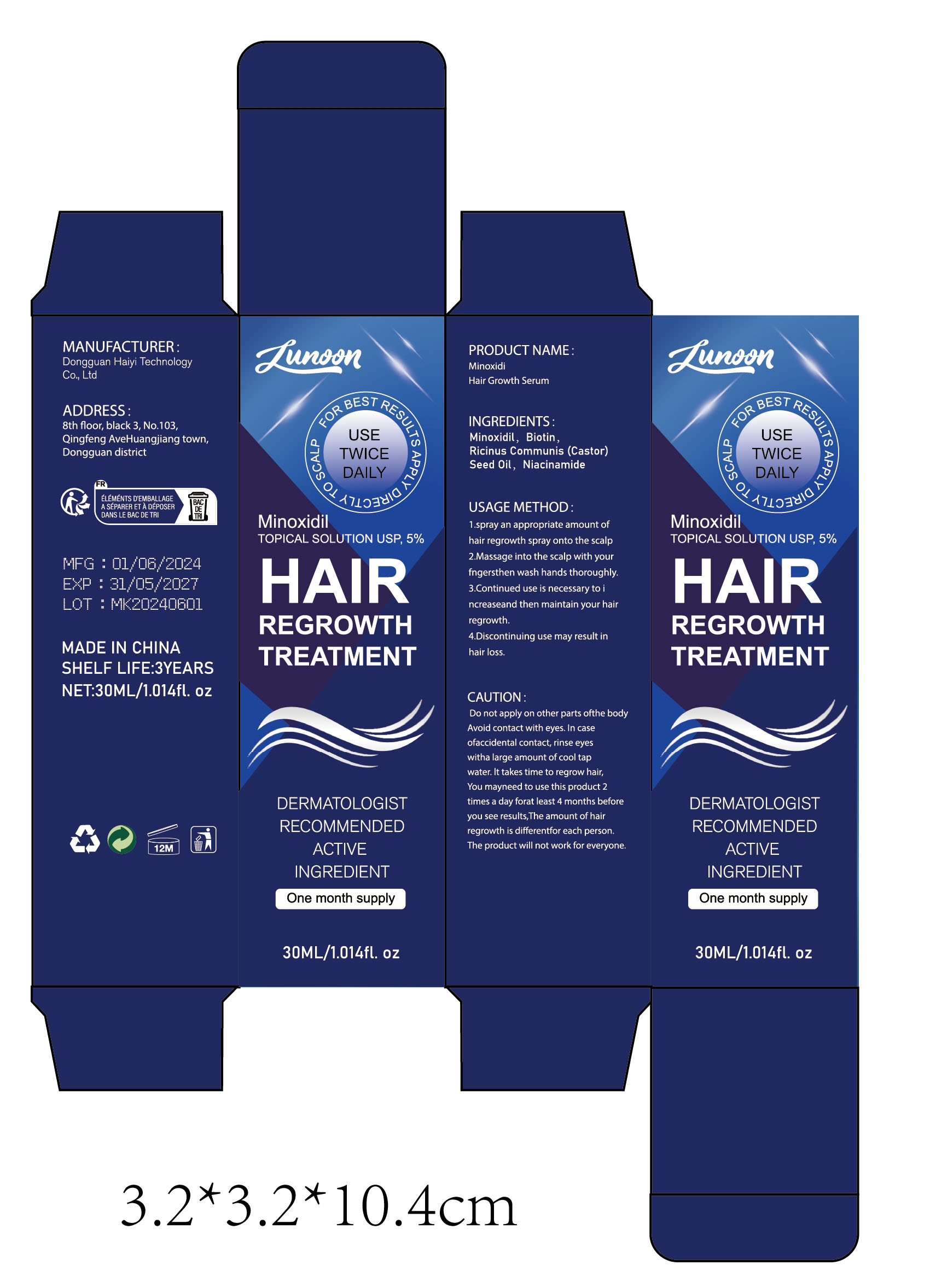 DRUG LABEL: Minoxidi Hair Growth Serum
NDC: 84732-025 | Form: SPRAY
Manufacturer: Dongguan Haiyi Technology Co.,Ltd.
Category: otc | Type: HUMAN OTC DRUG LABEL
Date: 20240929

ACTIVE INGREDIENTS: BIOTIN 1 mg/30 mL; MINOXIDIL 1 mg/30 mL; NIACINAMIDE 1 mg/30 mL
INACTIVE INGREDIENTS: CASTOR OIL

Active ingredient

Minoxidil

Biotin

Niacinamide

Inactive ingredient

Ricinus Communis (Castor) Seed Oil

Purpose section

HAIR REGROWTH TREATMENT

Warning

Do not apply on other parts ofthe body Avoid contact with eyes. In case ofaccidental contact, rinse eyes with a large amount of cool tap water. lt takes time to regrow hair,You mayneed to use this product 2times a day forat least 4 months before you see results,The amount of hair regrowth is different for each person.The product will not work for everyone.

stop use

This product may cause allergic reactions in asmall number of people.
lf youexperience any discomfort,please stop using it immediately.

not use

Not suitable for use by children, pregnantor breast feeding people.

OUT OF CHILDREN

KEEP THE PRODUCT OUT OF REACH OF CHILDREN to

HOW TO USE

1 .spray an appropriate amount ofhair regrowth spray onto the scalp

2.Massage into the scalp with yourfngersthen wash hands thoroughly.

3.Continued use is necessary to increaseand then maintain your hairregrowth.

4.Discontinuing use may result inhair loss.

Dosage

Apply 1 ml twice a day directly to the areas of hair loss on the scalp.